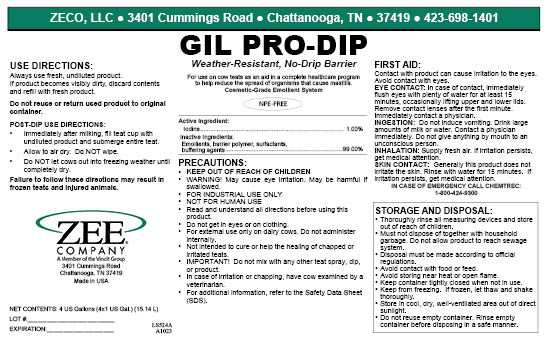 DRUG LABEL: Gil Pro-Dip
NDC: 86161-007 | Form: LIQUID
Manufacturer: ZECO, LLC
Category: animal | Type: OTC ANIMAL DRUG LABEL
Date: 20240124

ACTIVE INGREDIENTS: IODINE 10000 mg/1 L
INACTIVE INGREDIENTS: C12-16 PARETH-5; 4-NONYLPHENOL, BRANCHED; SODIUM BICARBONATE; GLYCERIN; XANTHAN GUM; PROPYLENE GLYCOL; NONOXYNOL-4

Gil Pro-Dip

USER SAFETY WARNINGS

Weather-Resistant, No-Drip Barrier

Cosmetic Grade Emollient System

For External Use Only on Dairy Cows

WARNING! May Cause Eye Irritation.

May Be Harmful If Swallowed.

Keep Out Of Reach Of Children

Use on each teat as an aid in a complete cow health care program to help reduce the spread of organisms that may cause mastitis.

Not intended to cure or help the healing of chapped or irritated teats.

In case of irritation or chapping, have cow examined by a veterinarian.

Active Ingredient

Iodine ............................................................................................... 1.00%

Inactive Ingredients

Emollients, barrier polymer, surfactants, and buffering agents.............. 99.00%

Important

Do NOT mix with any other eat spray, dip, or product.

Precautions

- KEEP FROM FREEZING. If frozen, let thaw and shake thoroughly.
- Do NOT get in eyes or on clothing. Do NOT take internally.
- Do NOT allow to contaminate food. Wash thoroughly after handling.
- Keep container tightly closed when not in use.
- Store in a cool, dry, well-ventilated area out of direct sunlight.

FIRST AID

EYES: Immediately flush eyes with plenty of water for at least 15 minutes occasionally lifting the upper and lower lids.
Contact a physician immediately.

INGESTION: Do NOT induce vomiting.
Drink large amounts of milk or water.
Contact a physician immediately.
Do not give anything by mouth to an unconscious person.

DOSAGE AND ADMINISTRATION

Post-Dip Use Directions

Always use fresh, undiluted product.
If product becomes visibly dirty, discard contents and refill with fresh product.
Do NOT reuse or return used product to original container.

Immediately after milking, fill teat cup with undiluted product and submerge entire teat.
Allow to air dry—do NOT wipe.
Do NOT let cows out in freezing weather until completely dry.

PACKAGE LABEL

Add image transcription here...